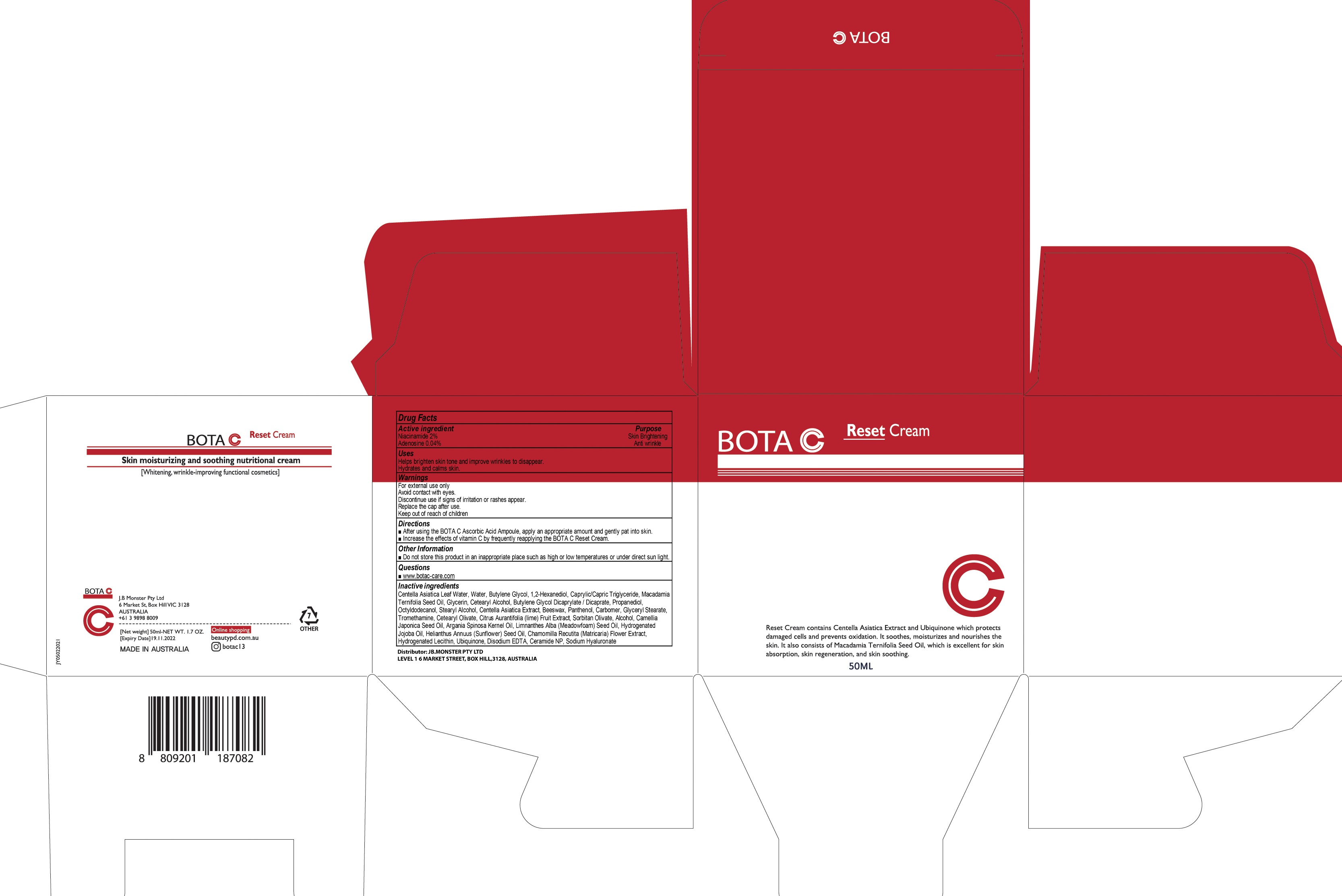 DRUG LABEL: BOTA C Reset
NDC: 82399-010 | Form: CREAM
Manufacturer: JB.MONSTER PTY LTD
Category: otc | Type: HUMAN OTC DRUG LABEL
Date: 20211126

ACTIVE INGREDIENTS: Niacinamide 1.0 g/50 mL; Adenosine 0.02 g/50 mL
INACTIVE INGREDIENTS: CENTELLA ASIATICA LEAF; Water; Butylene Glycol

ACTIVE INGREDIENTS

Niacinamide 2%
Adenosine 0.04%

INACTIVE INGREDIENTS

Centella Asiatica Leaf Water, Water, Butylene Glycol, 1,2-Hexanediol, Caprylic/Capric Triglyceride, Macadamia Ternifolia Seed Oil, Glycerin,
Cetearyl Alcohol, Butylene Glycol Dicaprylate / Dicaprate, Propanediol, Octyldodecanol, Stearyl Alcohol, Centella Asiatica Extract, Beeswax, Panthenol, Carbomer, Glyceryl Stearate, Tromethamine, Cetearyl Olivate, Citrus Aurantifolia (lime) Fruit Extract, Sorbitan Olivate, Alcohol, Camellia Japonica Seed Oil, Argania Spinosa Kernel Oil, Limnanthes Alba (Meadowfoam) Seed Oil, Hydrogenated Jojoba Oil, Helianthus Annuus (Sunflower) Seed Oil, Chamomilla Recutita (Matricaria) Flower Extract, Hydrogenated Lecithin, Ubiquinone, Disodium EDTA, Ceramide NP, Sodium Hyaluronate

PURPOSE

Skin Brightening
Anti wrinkle

Uses

■ Helps brighten skin tone and improve wrinkles to disappear.
■ Hydrates and calms skin.

WARNINGS

For external use only
Avoid contact with eyes.
Discontinue use if signs of irritation or rashes appear.
Replace the cap after use.
Keep out of reach of children

KEEP OUT OF REACH OF CHILDREN

Directions

■ After using the BOTA C Ascorbic Acid Ampoule, apply an appropriate amount and gently pat into skin.
■ Increase the effects of vitamin C by frequently reapplying the BOTA C Reset Cream.

Other Information

■ Do not store this product in an inappropriate place such as high or low temperatures or under direct sun light

Questions

■ www.botac-care.com